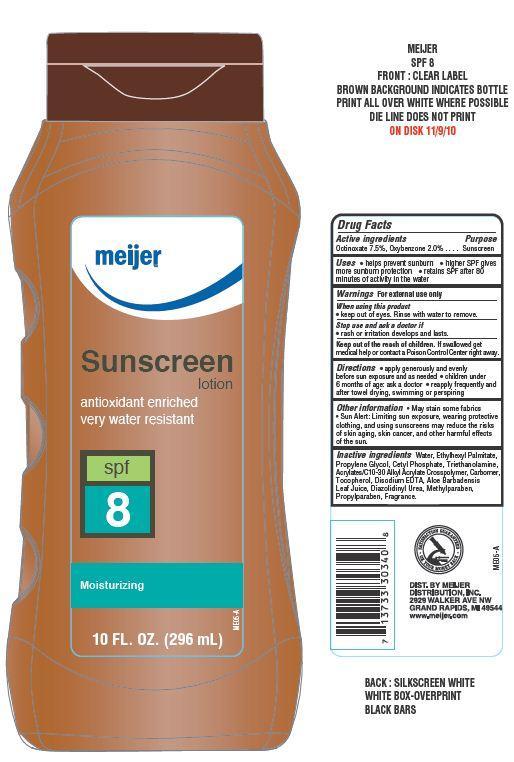 DRUG LABEL: Meijer Suscreen SPF 8
NDC: 41250-023 | Form: LOTION
Manufacturer: Meijer Distribution Inc
Category: otc | Type: HUMAN OTC DRUG LABEL
Date: 20130701

ACTIVE INGREDIENTS: OCTINOXATE 7.5 g/100 g; OXYBENZONE 2 g/100 g
INACTIVE INGREDIENTS: WATER; ETHYLHEXYL PALMITATE; PROPYLENE GLYCOL; CETYL PHOSPHATE; TROLAMINE; TOCOPHEROL; EDETATE DISODIUM; ALOE VERA LEAF; DIAZOLIDINYL UREA; METHYLPARABEN; PROPYLPARABEN

Drug Facts

Active ingredients

Octinoxate 7.5%

Oxybenzone 2.0%

Uses

- helps prevent suburn
- higher SPF gives more sunburn protection
- retains SPF after 80 minutes of activity in water

Warnings

For external use only

When using this product

- keep out of eyes. Rinse with water to remove

Stop use and ask a doctor if

- rash or irritation develops and lasts

KEEP OUT OF REACH OF CHILDREN

Keep out of the reach of children. If swallowed get medical help or contact a Poison Control Center right away.

Directions

- apply generously and evenly before sun exposure and as needed
- children under 6 months of age: ask a doctor
- reapply frequently and after towel drying, swimming or perspiring

Other information

- may stain some fabrics
- Sun Alert: Limiting sun exposure, wearing protective clothing, and using sunscreens may reduce the risks of skin aging, skin cancer and other harmful effects of the sun

Inactive ingredients

Water, Ethylhexyl Palmitate, Propylene Glycol, Cetyl Phosphate, Triethanolamine, Acrylates/C10-30 Alkyl Acrylate Crosspolymer, Carbomer, Tocopherol, Disodium EDTA, Aloe Barbadensis Leaf Juice Powder, Diazolidinyl Urea, Methylparaben, Propylparaben, Fragrance.

Principal Display Panel

meijer

Sunscreen lotion

antioxidant enriched

spf 8

Moisturizing

10 FL. OZ. (296 mL)

Purpose

Sunscreen